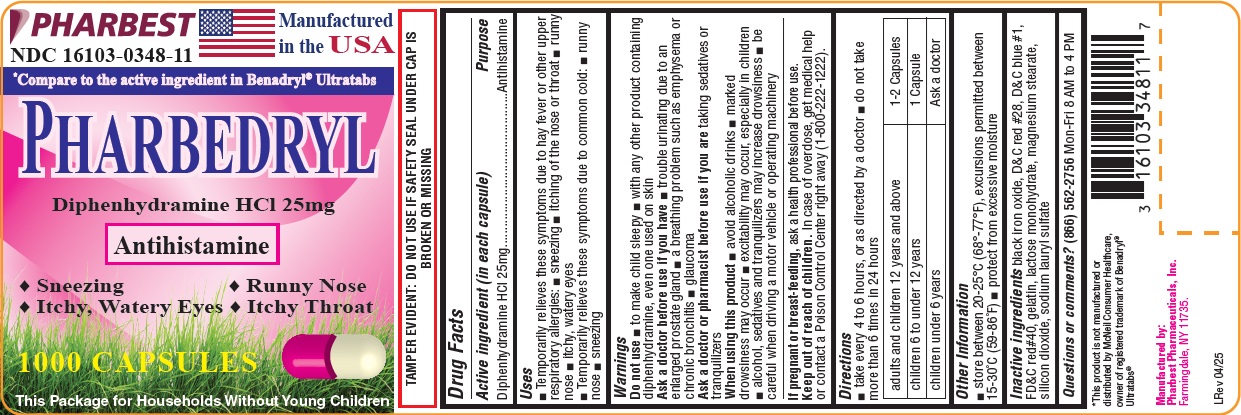 DRUG LABEL: Pharbedryl     
NDC: 16103-348 | Form: CAPSULE
Manufacturer: Pharbest Pharmaceuticals, Inc.
Category: otc | Type: HUMAN OTC DRUG LABEL
Date: 20251224

ACTIVE INGREDIENTS: DIPHENHYDRAMINE HYDROCHLORIDE 25 mg/1 1
INACTIVE INGREDIENTS: FERROSOFERRIC OXIDE ; D&C RED NO. 28; FD&C BLUE NO. 1; FD&C RED NO. 40; GELATIN, UNSPECIFIED; LACTOSE MONOHYDRATE; MAGNESIUM STEARATE ; SILICON DIOXIDE; SODIUM LAURYL SULFATE 

Drug Facts

Active ingredient (in each capsule)

Diphenhydramine HCl 25mg

Purpose

Antihistamine

Uses

- Temporarily relieves these symptoms due to hay fever or other respiratory allergies:
- sneezing
- itching of the nose or throat
- runny nose
- itchy, watery eyes
- Temporarily relieves these symptoms due to common cold:
- runny nose
- sneezing

Warnings

Do not use

- to make child sleepy
- with any other product containing diphenhydramine, even one used on skin

Ask a doctor before use if you have

- trouble urinating due to an enlarged prostate gland
- a breathing problem such as emphysema or chronic bronchitis
- glaucoma

Ask a doctor or pharmacist before use if you are

taking sedatives or tranquilizers

When using this product

- avoid alcoholic drinks
- marked drowsiness may occur
- excitability may occur, especially in children
- alcohol, sedatives and tranquilizers may increase drowsiness
- be careful when driving a motor vehicle or operating machinery

If pregnant or breast-feeding,

ask a health professional before use.

Keep out of reach of children.

(In case of overdose, get medical help or contact a Poison Control Center right away (1-800-222-1222).

Directions

- take every 4 to 6 hours, or as directed by a doctor
- do not take more than 6 times in 24 hours

adults and children 12 years and above | 1-2 Capsules
children 6 to under 12 years | 1 Capsule
children under 6 years | Ask a doctor

Other information

- store between 20°-25°C (68°-77°F), excursions permitted between 15-30°C (59-86°F)
- protect from excessive moisture

Inactive ingredients

black iron oxide, D&C red #28, D&C blue #1, FD&C red #40, gelatin, lactose monohydrate, magnesium stearate, silicon dioxide, sodium lauryl sulfate

Questions or comments?

(866)562-2756 Mon - Fri 8 AM to 4 PM

PACKAGE LABEL

PHARBEST

NDC 16103-0348-11

Manufactured in the USA

* Compare to the active ingredient in Benadryl® Ultratabs

PHARBEDRYL

Diphenhydramine HCl 25mg

Antihistamine

• Sneezing • Runny Nose

• Itchy, Watery Eyes • Itchy Throat

1000 CAPSULES

This Package for Households without Young Childern